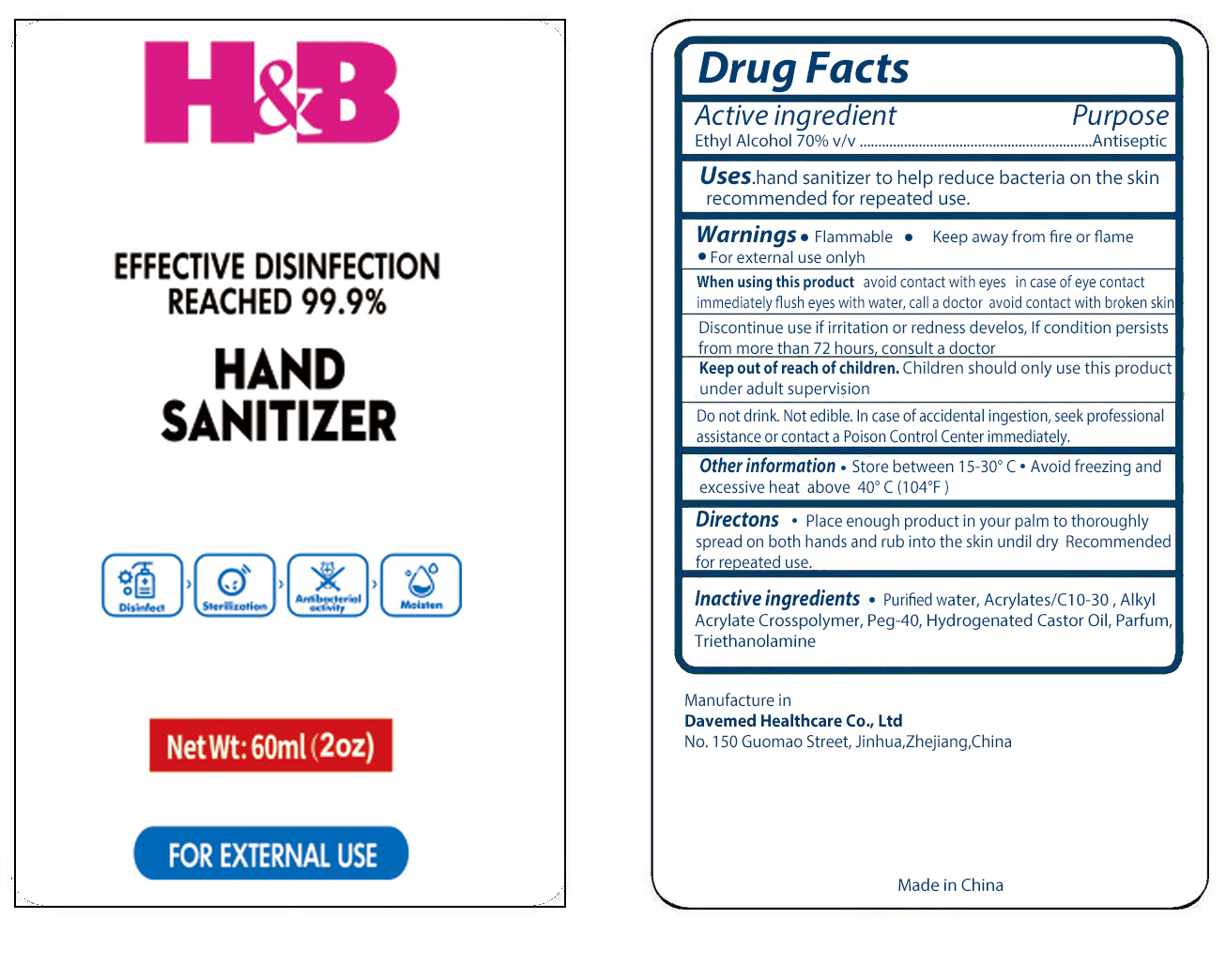 DRUG LABEL: Hand Sanitizer
NDC: 70897-012 | Form: GEL
Manufacturer: Davemed Healthcare Co., Ltd
Category: otc | Type: HUMAN OTC DRUG LABEL
Date: 20200730

ACTIVE INGREDIENTS: ALCOHOL 70 mL/100 mL
INACTIVE INGREDIENTS: CARBOMER INTERPOLYMER TYPE A (ALLYL SUCROSE CROSSLINKED); WATER; HYDROGENATED CASTOR OIL; TROLAMINE; PEG-40 SORBITAN DIISOSTEARATE

Hand Sanitizer Davemed Healthcare Co., Ltd

Active Ingredient

Ethyl Alcohol 70% v/v

USES

To decrease bacteria on the skin that could cause disease.

Recommended for repeated use.

WARNING:

Flammable.

Keep away from fire or flame.

For external use of onlyh.

WHEN USING THIS PRODUCT:

avoid contact with eyes in case of eye contact immediately flush eyes with water, call a doctor avoid contact with broken skin.

STOP USE AND ASK A DOCTOR:

Discontinue use if irritation or redness develos, If condition persists from more than 72 hours, consult a doctor

KEEP OUT OF CHILDREN:

Children should only use this product under adult supervision

DIRECTIONS:

- Place enough product in your palm to thoroughly spread on both hands and rub into the skin undil dry Recommended for repeated use.

INGREDIENTS:

Water, Alcohol, Acrylates/C10-30 Alkyl Acrylate Crosspolymer, Peg-40, Hydrogenated Castor Oil, Parfum, Triethanolamine

PURPOSE

Antiseptic

OTHER SAFETY INFORMATION

Do not drink. Not edible. In case of accidental ingestion, seek professional assistance or contact a Poison Control Center immediately

OTHER SAFETY INFORMATION

- Store between 15-30C
- Avoid freezing and excessive heat above 40C (104F)